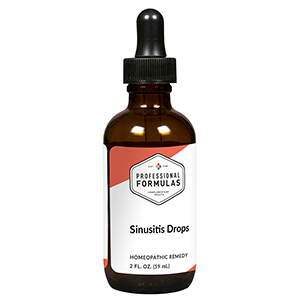 DRUG LABEL: Sinusitis Drops
NDC: 63083-2060 | Form: LIQUID
Manufacturer: Professional Complementary Health Formulas
Category: homeopathic | Type: HUMAN OTC DRUG LABEL
Date: 20190815

ACTIVE INGREDIENTS: BLACK MUSTARD SEED 3 [hp_X]/59 mL; PULSATILLA MONTANA WHOLE 4 [hp_X]/59 mL; EUPHORBIA RESINIFERA RESIN 6 [hp_X]/59 mL; CALCIUM SULFIDE 6 [hp_X]/59 mL; POTASSIUM DICHROMATE 6 [hp_X]/59 mL; LUFFA OPERCULATA FRUIT 6 [hp_X]/59 mL; SILICON DIOXIDE 6 [hp_X]/59 mL; GUAIAC 8 [hp_X]/59 mL; MERCURIC SULFIDE 12 [hp_X]/59 mL
INACTIVE INGREDIENTS: ALCOHOL; WATER

C60

ACTIVE INGREDIENTS

Sinapis nigra 3X
Pulsatilla 4X
Euphorbium officinarum 6X
Hepar sulphuris calcareum 6X
Kali bichromicum 6X
Luffa operculata 6X
Silicea 6X
Guaiacum 8X
Cinnabaris 12X

QUESTIONS

Professional Formulas

PO Box 2034 Lake Oswego, OR 97035

INDICATIONS

For the temporary relief of runny nose, nasal congestion, headache, or mild facial or ear pain due to a cold, hay fever, or other upper respiratory allergies.*

PURPOSE

*Claims based on traditional homeopathic practice, not accepted medical evidence. Not FDA evaluated.

WARNINGS

If symptoms do not improve or are accompanied by fever, consult a doctor. Keep out of the reach of children. In case of overdose, get medical help or contact a poison control center right away. If pregnant or breastfeeding, ask a healthcare professional before use.

Keep out of the reach of children.

PREGNANCY OR BREAST FEEDING

If pregnant or breastfeeding, ask a healthcare professional before use.

DIRECTIONS

Place drops under tongue 30 minutes before/after meals. Adults and children 12 years and over: Take 10 drops up to 3 times per day for up to 6 weeks. For immediate onset of symptoms, take 10 to 15 drops every 15 minutes up to 3 hours. For less severe symptoms, take 10-15 drops hourly up to 8 hours. Consult a physician for use in children under 12 years of age.

OTHER INFORMATION

Tamper resistant. If seal is broken, do not use. After opening, close container tightly and store at room temperature away from heat.

INACTIVE INGREDIENTS

20% ethanol, purified water.

LABEL

Est 1985

Professional Formulas

Complementary Health

Sinusitis Drops

Homeopathic Remedy

2 FL. OZ. (59 mL)